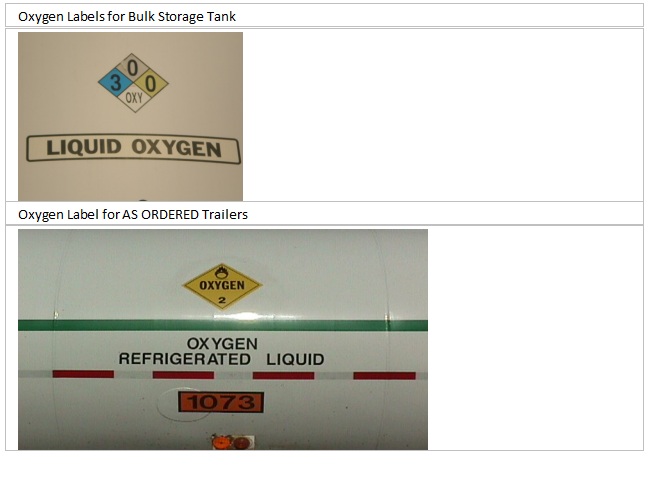 DRUG LABEL: Oxygen
NDC: 49390-100 | Form: GAS
Manufacturer: Linweld, Inc.
Category: prescription | Type: HUMAN PRESCRIPTION DRUG LABEL
Date: 20091117

ACTIVE INGREDIENTS: Oxygen 995 mL/1 L

Oxygen Label

PACKAGE LABEL

Enter section text here

Oxygen Labels for Bulk Storage Tank

300 OXY

LIQUID OXYGEN

Oxygen Label for AS ORDERED Trailers

Oxygen 2

OXYGEN REFRIGERATED LIQUID

1073